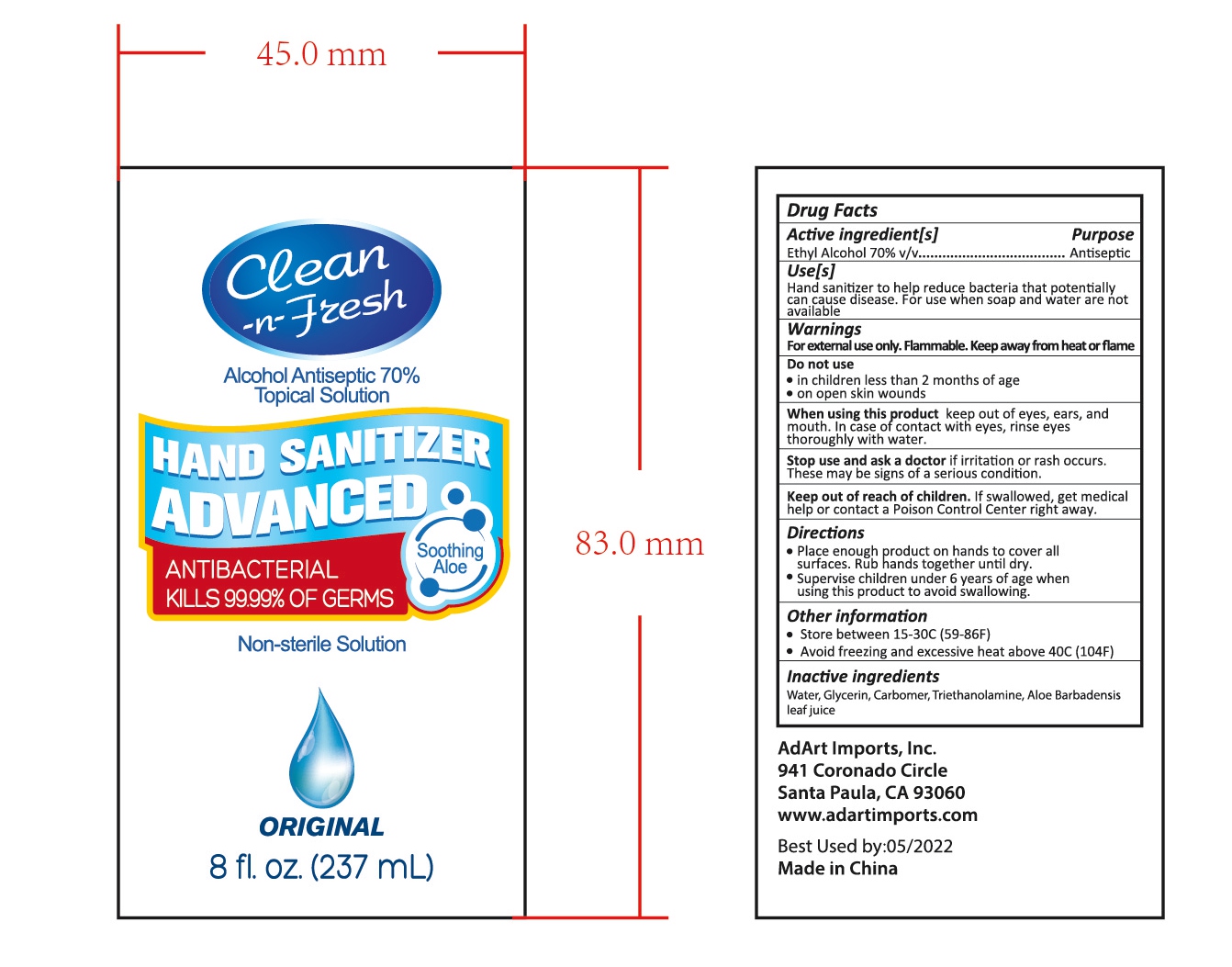 DRUG LABEL: HAND SANITIZER
NDC: 47993-259 | Form: GEL
Manufacturer: NINGBO JIANGBEI OCEAN STAR TRADING CO.,LTD
Category: otc | Type: HUMAN OTC DRUG LABEL
Date: 20201104

ACTIVE INGREDIENTS: ALCOHOL 70 mL/100 mL
INACTIVE INGREDIENTS: ALOE VERA LEAF; GLYCERIN; WATER; TRIETHANOLAMINE BENZOATE; CARBOMER 940

47993-259

Active ingredients

Ethyl Alcohol 70% v/v

PURPOSE

Antiseptic

Uses：

Hands sanitizer to help reduce bacteria that potentially can cause disease. For use when soap and water are not available.

Warnings:

For external use only. Flammable. keep away from fire or flame.

Do not use

- In children less than 2 months of age.
- On open skin wounds.

When using this product.

Keep out of eyes, ears, and mouth. In case of contact with eyes，rinse eyes thoroughly with water.

Stop use and ask a doctor

if irritation or rash occurs. These may be signs of a serious condition.

Keep out of reach of children.

If swallowed, get medical help or contact a Poison Control Center right away.

Directions:

- Place enough product on hands to cover all surfaces. Rub hands together until dry.
- Supervise children under 6 years of age when using this product to avoid swallowing.

Other information

- Store between 15-30℃（59-86℉）
- Avoid freezing and excessive heat above 40℃（104℉）

Inactive Ingredients:

Water,Glycerin,Carbomer,Triethanolamine,Aloe Barbadensis leaf juice